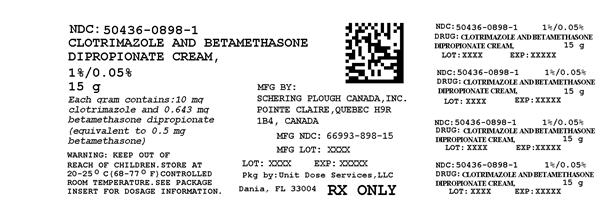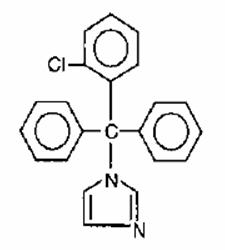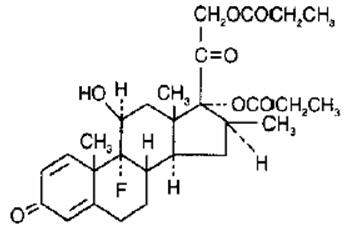 DRUG LABEL: Clotrimazole and Betamethasone Dipropionate
NDC: 50436-0898 | Form: CREAM
Manufacturer: Unit Dose Services
Category: prescription | Type: HUMAN PRESCRIPTION DRUG LABEL
Date: 20160704

ACTIVE INGREDIENTS: CLOTRIMAZOLE 10 mg/1 g; BETAMETHASONE DIPROPIONATE 0.5 mg/1 g
INACTIVE INGREDIENTS: WATER; MINERAL OIL; PETROLATUM; CETYL ALCOHOL; STEARYL ALCOHOL; CETEARETH-30; PROPYLENE GLYCOL; SODIUM PHOSPHATE, MONOBASIC, MONOHYDRATE; PHOSPHORIC ACID; BENZYL ALCOHOL; SODIUM HYDROXIDE

HIGHLIGHTS OF PRESCRIBING INFORMATION

These highlights do not include all the information needed to use clotrimazole and betamethasone dipropionate cream safely and effectively. See full prescribing information for clotrimazole and betamethasone dipropionate cream.
Clotrimazole and betamethasone dipropionate cream, 1%/0.05%, for topical use
Initial U.S. Approval: 1984

1 INDICATIONS AND USAGE

Clotrimazole and Betamethasone Dipropionate cream contains a combination of clotrimazole, an azole antifungal, and betamethasone dipropionate, a corticosteroid, and is indicated for the topical treatment of symptomatic inflammatory tinea pedis, tinea cruris, and tinea corporis due to Epidermophyton floccosum, Trichophyton mentagrophytes, and Trichophyton rubrum in patients 17 years and older. (1)

2 DOSAGE AND ADMINISTRATION

- Tinea pedis: Apply a thin film to the affected skin areas twice a day for 2 weeks. (2)
- Tinea cruris and tinea corporis: Apply a thin film to the affected skin area twice a day for 1 week. (2)
- Clotrimazole and Betamethasone Dipropionate cream should not be used longer than 2 weeks in the treatment of tinea corporis or tinea cruris, and longer than 4 weeks in the treatment of tinea pedis. (2)
- Do not use with occlusive dressings unless directed by a physician. (2)
- Not for ophthalmic, oral or intravaginal use. (2)

3 DOSAGE FORMS AND STRENGTHS

Cream, 1%/0.05% (3)

Each gram of clotrimazole and betamethasone dipropionate cream contains 10 mg of clotrimazole and 0.643 mg of betamethasone dipropionate (equivalent to 0.5 mg of betamethasone) (3)

4 CONTRAINDICATIONS

None. (4)

5 WARNINGS AND PRECAUTIONS

- Clotrimazole and Betamethasone Dipropionate cream can cause reversible HPA axis suppression with the potential for glucocorticosteroid insufficiency during and after withdrawal of the treatment. Risk factor(s) are: use of high-potency topical corticosteroid, use over a large surface area or to areas under occlusion, prolonged use, altered skin barrier, liver failure, and young age. Modify use should HPA axis suppression develop. (5.1, 8.4)
- Pediatric patients may be more susceptible to systemic toxicity. (5.1, 8.4)
- The use of clotrimazole and betamethasone dipropionate cream in the treatment of diaper dermatitis is not recommended. (5.2)

6 ADVERSE REACTIONS

Most common adverse reactions reported for clotrimazole and betamethasone dipropionate cream were paraesthesia in 1.9% of patients and rash, edema, and secondary infections each in less than 1% of patients. (6.1)

To report SUSPECTED ADVERSE REACTIONS, contact Merck Sharp & Dohme Corp., a subsidiary of Merck & Co., Inc., at 1-877-888-4231 or FDA at 1-800-FDA-1088 or www.fda.gov/medwatch.

FULL PRESCRIBING INFORMATION

1 INDICATIONS AND USAGE

Clotrimazole and Betamethasone Dipropionate cream is a combination of an azole antifungal and corticosteroid and is indicated for the topical treatment of symptomatic inflammatory tinea pedis, tinea cruris, and tinea corporis due to Epidermophyton floccosum, Trichophyton mentagrophytes, and Trichophyton rubrum in patients 17 years and older.

2 DOSAGE AND ADMINISTRATION

Treatment of tinea corporis or tinea cruris:

- Apply a thin film of clotrimazole and betamethasone dipropionate cream into the affected skin areas twice a day for one week.
- Do not use more than 45 grams per week. Do not use with occlusive dressings.
- If a patient shows no clinical improvement after 1 week of treatment with clotrimazole and betamethasone dipropionate cream, the diagnosis should be reviewed.
- Do not use longer than 2 weeks.

Treatment of tinea pedis:

- Gently massage a sufficient amount of clotrimazole and betamethasone dipropionate cream into the affected skin areas twice a day for two weeks.
- Do not use more than 45 grams per week. Do not use with occlusive dressings.
- If a patient shows no clinical improvement after 2 weeks of treatment with clotrimazole and betamethasone dipropionate cream, the diagnosis should be reviewed.
- Do not use longer than 4 weeks.

Clotrimazole and Betamethasone Dipropionate cream is for topical use only. It is not for oral, ophthalmic, or intravaginal use.

3 DOSAGE FORMS AND STRENGTHS

Cream, 1%/0.05%. Each gram of clotrimazole and betamethasone dipropionate cream contains 10 mg of clotrimazole and 0.643 mg of betamethasone dipropionate (equivalent to 0.5 mg of betamethasone) in a white to off-white cream base.

4 CONTRAINDICATIONS

None.

5 WARNINGS AND PRECAUTIONS

5.1 Effects on Endocrine System

Clotrimazole and Betamethasone Dipropionate cream can cause reversible hypothalamic-pituitary-adrenal (HPA) axis suppression with the potential for glucocorticosteroid insufficiency. This may occur during treatment or after withdrawal of treatment. Cushing's syndrome and hyperglycemia may also occur due to the systemic effect of corticosteroids while on treatment. Factors that predispose a patient to HPA axis suppression include the use of high-potency steroids, large treatment surface areas, prolonged use, use of occlusive dressing, altered skin barrier, liver failure, and young age.

Because of the potential for systemic corticosteroid effects, patients may need to be periodically evaluated for HPA axis suppression. This may be done by using the adrenocorticotropic hormone (ACTH) stimulation test.

In a small trial, clotrimazole and betamethasone dipropionate cream was applied using large dosages, 7 g daily for 14 days (BID) to the crural area of normal adult subjects. Three of the 8 normal subjects on whom clotrimazole and betamethasone dipropionate cream was applied exhibited low morning plasma cortisol levels during treatment. One of these subjects had an abnormal cosyntropin test. The effect on morning plasma cortisol was transient and subjects recovered 1 week after discontinuing dosing. In addition, 2 separate trials in pediatric subjects demonstrated adrenal suppression as determined by cosyntropin testing [see Use in Specific Populations (8.4)].

If HPA axis suppression is documented, gradually withdraw the drug, reduce the frequency of application, or substitute with a less potent corticosteroid.

Pediatric patients may be more susceptible to systemic toxicity due to their larger skin-surface-to-body mass ratios [see Use in Specific Populations (8.4)].

5.2 Diaper Dermatitis

The use of clotrimazole and betamethasone dipropionate cream in the treatment of diaper dermatitis is not recommended.

6 ADVERSE REACTIONS

6.1 Clinical Trial Experience

Because clinical trials are conducted under widely varying conditions, adverse reaction rates observed in the clinical trials of a drug cannot be directly compared to rates in the clinical trials of another drug and may not reflect the rates observed in practice.

In clinical trials common adverse reaction reported for clotrimazole and betamethasone dipropionate cream was paresthesia in 1.9% of patients. Adverse reactions reported at a frequency < 1% included rash, edema, and secondary infection.

6.2 Postmarketing Experience

Because adverse reactions are reported voluntarily from a population of uncertain size, it is not always possible to reliably estimate their frequency or establish a causal relationship to drug exposure.

The following local adverse reactions have been reported with topical corticosteroids: itching, irritation, dryness, folliculitis, hypertrichosis, acneiform eruptions, hypopigmentation, perioral dermatitis, allergic contact dermatitis, maceration of the skin, skin atrophy, striae, miliaria, capillary fragility (ecchymoses), telangiectasia, and sensitization (local reactions upon repeated application of product).

Adverse reactions reported with the use of clotrimazole are: erythema, stinging, blistering, peeling, edema, pruritus, urticaria, and general irritation of the skin.

8 USE IN SPECIFIC POPULATIONS

8.1 Pregnancy

Teratogenic effects,

Pregnancy Category C

There are no adequate and well-controlled studies with clotrimazole and betamethasone dipropionate cream in pregnant women. Therefore, clotrimazole and betamethasone dipropionate cream should be used during pregnancy only if the potential benefit justifies the potential risk to the fetus.

There have been no teratogenic studies performed in animals or humans with the combination of clotrimazole and betamethasone dipropionate. Corticosteroids are generally teratogenic in laboratory animals when administered at relatively low dosage levels.

Studies in pregnant rats with intravaginal doses up to 100 mg/kg (15 times the maximum human dose) revealed no evidence of fetotoxicity due to clotrimazole exposure.

No increase in fetal malformations was noted in pregnant rats receiving oral (gastric tube) clotrimazole doses up to 100 mg/kg/day during gestation Days 6 to 15. However, clotrimazole dosed at 100 mg/kg/day was embryotoxic (increased resorptions), fetotoxic (reduced fetal weights), and maternally toxic (reduced body weight gain) to rats. Clotrimazole dosed at 200 mg/kg/day (30 times the maximum human dose) was maternally lethal, and therefore, fetuses were not evaluated in this group. Also in this study, doses up to 50 mg/kg/day (8 times the maximum human dose) had no adverse effects on dams or fetuses. However, in the combined fertility, teratogenicity, and postnatal development study described above, 50 mg/kg clotrimazole was associated with reduced maternal weight gain and reduced numbers of offspring reared to 4 weeks.

Oral clotrimazole doses of 25, 50, 100, and 200 mg/kg/day (2-15 times the maximum human dose) were not teratogenic in mice. No evidence of maternal toxicity or embryotoxicity was seen in pregnant rabbits dosed orally with 60, 120, or 180 mg/kg/day (18-55 times the maximum human dose).

Betamethasone dipropionate has been shown to be teratogenic in rabbits when given by the intramuscular route at doses of 0.05 mg/kg. This dose is approximately one-fifth the maximum human dose. The abnormalities observed included umbilical hernias, cephalocele, and cleft palates.

Betamethasone dipropionate has not been tested for teratogenic potential by the dermal route of administration. Some corticosteroids have been shown to be teratogenic after dermal application to laboratory animals.

8.3 Nursing Mothers

Systemically administered corticosteroids appear in human milk and can suppress growth, interfere with endogenous corticosteroid production, or cause other untoward effects. It is not known whether topical administration of corticosteroids can result in sufficient systemic absorption to produce detectable quantities in human milk. Because many drugs are excreted in human milk, caution should be exercised when clotrimazole and betamethasone dipropionate cream is administered to a nursing woman.

8.4 Pediatric Use

The use of clotrimazole and betamethasone dipropionate cream in patients under 17 years of age is not recommended.

Adverse events consistent with corticosteroid use have been observed in pediatric patients treated with clotrimazole and betamethasone dipropionate cream. In open-label trials, 17 of 43 (39.5%) evaluable pediatric subjects (aged 12-16 years old) using clotrimazole and betamethasone dipropionate cream for treatment of tinea pedis demonstrated adrenal suppression as determined by cosyntropin testing. In another open-label trial, 8 of 17 (47.1%) evaluable pediatric subjects (aged 12-16 years old) using clotrimazole and betamethasone dipropionate cream for treatment of tinea cruris demonstrated adrenal suppression as determined by cosyntropin testing.

Because of a higher ratio of skin surface area to body mass, pediatric patients are at a greater risk than adults of HPA axis suppression when they are treated with topical corticosteroids. They are, therefore also at greater risk of adrenal insufficiency during and/or after withdrawal of treatment. Pediatric patients may be more susceptible than adults to skin atrophy, including striae, when they are treated with topical corticosteroids.

HPA axis suppression, Cushing's syndrome, linear growth retardation, delayed weight gain, and intracranial hypertension have been reported in pediatric patients receiving topical corticosteroids [see Warnings and Precautions (5.1)].

Avoid use of clotrimazole and betamethasone dipropionate cream in the treatment of diaper dermatitis.

8.5 Geriatric Use

Clinical studies of clotrimazole and betamethasone dipropionate cream did not include sufficient numbers of subjects aged 65 and over to determine whether they respond differently from younger subjects. However, greater sensitivity of some older individuals cannot be ruled out. The use of clotrimazole and betamethasone dipropionate cream under occlusion, such as in diaper dermatitis, is not recommended.

Postmarket adverse event reporting for clotrimazole and betamethasone dipropionate cream in patients aged 65 and above includes reports of skin atrophy and rare reports of skin ulceration. Caution should be exercised with the use of these corticosteroid-containing topical products on thinning skin.

11 DESCRIPTION

Clotrimazole and betamethasone dipropionate cream, 1%/0.05%, contains combinations of clotrimazole, an azole antifungal, and betamethasone dipropionate, a corticosteroid, for topical use.

Chemically, clotrimazole is 1–(o-chloro-α,α-diphenylbenzyl) imidazole, with the empirical formula C22H17CLN2, a molecular weight of 344.84, and the following structural formula:

Clotrimazole is an odorless, white crystalline powder, insoluble in water and soluble in ethanol.

Betamethasone dipropionate has 9-fluoro-11β,17,21-trihydroxy-16β-methylpregna-1,4-diene-3,20-dione 17,21-dipropionate, with the empirical formula C28H37FO7, a molecular weight of 504.59, and the following structural formula:

Betamethasone dipropionate is a white to creamy-white, odorless crystalline powder, insoluble in water.

Each gram of clotrimazole and betamethasone dipropionate cream contains 10 mg clotrimazole and 0.643 mg betamethasone dipropionate (equivalent to 0.5 mg betamethasone), in a white to off-white, hydrophilic cream consisting of benzyl alcohol as a preservative, ceteareth-30, cetyl alcohol plus stearyl alcohol, mineral oil, phosphoric acid, propylene glycol, purified water, sodium phosphate monobasic monohydrate, and white petrolatum.

12 CLINICAL PHARMACOLOGY

12.1 Mechanism of Action

Clotrimazole is an azole antifungal [see Clinical Pharmacology (12.4)].

Betamethasone dipropionate is a corticosteroid. Corticosteroids play a role in cellular signaling, immune function, inflammation, and protein regulation; however, the precise mechanism of action for the treatment of tinea pedis, tinea cruris and tinea corporis is unknown.

12.2 Pharmacodynamics

Vasoconstrictor Assay:

Studies performed with clotrimazole and betamethasone dipropionate cream indicate that these topical combination antifungal/corticosteroids may have vasoconstrictor potencies in a range that is comparable to high-potency topical corticosteroids. However, similar blanching scores do not necessarily imply therapeutic equivalence.

12.3 Pharmacokinetics

Skin penetration and systemic absorption of clotrimazole and betamethasone dipropionate following topical application of clotrimazole and betamethasone dipropionate cream has not been studied.

The extent of percutaneous absorption of topical corticosteroids is determined by many factors, including the vehicle, the integrity of the epidermal barrier, and the use of occlusive dressings. Topical corticosteroids can be absorbed from normal intact skin. Inflammation and/or other disease processes in the skin may increase percutaneous absorption of topical corticosteroids. Occlusive dressings substantially increase the percutaneous absorption of topical corticosteroids [see Dosage and Administration (2)].

Once absorbed through the skin, the pharmacokinetics of topical corticosteroids are similar to systemically administered corticosteroids. Corticosteroids are bound to plasma proteins in varying degrees. Corticosteroids are metabolized primarily in the liver and are then excreted by the kidneys. Some of the topical corticosteroids and their metabolites are also excreted into the bile.

12.4 Microbiology

Mechanism of Action:

Clotrimazole, an azole antifungal agent, inhibits 14-α-demethylation of lanosterol in fungi by binding to one of the cytochrome P-450 enzymes. This leads to the accumulation of 14-α-methylsterols and reduced concentrations of ergosterol, a sterol essential for a normal fungal cytoplasmic membrane. The methylsterols may affect the electron transport system, thereby inhibiting growth of fungi.

Activity In Vitro and In Vivo:

Clotrimazole has been shown to be active against most strains of the following dermatophytes, both in vitro and in clinical infections, Epidermophyton floccosum, Trichophyton mentagrophytes, and Trichophyton rubrum [see Indications and Usage (1)].

Drug Resistance:

Strains of dermatophytes having a natural resistance to clotrimazole have not been reported. Resistance to azoles, including clotrimazole, has been reported in some Candida species.

No single-step or multiple-step resistance to clotrimazole has developed during successive passages of Trichophyton mentagrophytes.

13 NONCLINICAL TOXICOLOGY

13.1 Carcinogenesis, Mutagenesis, Impairment of Fertility

There are no adequate laboratory animal studies with either the combination of clotrimazole and betamethasone dipropionate or with either component individually to evaluate carcinogenesis.

Betamethasone was negative in the bacterial mutagenicity assay (Salmonella typhimurium and Escherichia coli) and in the mammalian cell mutagenicity assay (CHO/HGPRT). It was positive in the in vitro human lymphocyte chromosome aberration assay, and equivocal in the in vivo mouse bone marrow micronucleus assay.

Reproductive studies with betamethasone dipropionate carried out in rabbits at doses of 1.0 mg/kg by the intramuscular route and in mice up to 33 mg/kg by the intramuscular route indicated no impairment of fertility except for dose-related increases in fetal resorption rates in both species. These doses are approximately 5- and 38-fold the maximum human dose based on body surface areas, respectively.

In a combined study of the effects of clotrimazole on fertility, teratogenicity, and postnatal development, male and female rats were dosed orally (diet admixture) with levels of 5, 10, 25, or 50 mg/kg/day (approximately 1-8 times the maximum dose in a 60-kg adult based on body surface area) from 10 weeks prior to mating until 4 weeks postpartum. No adverse effects on the duration of estrous cycle, fertility, or duration of pregnancy were noted.

14 CLINICAL STUDIES

In clinical trials of tinea corporis, tinea cruris, and tinea pedis, subjects treated with clotrimazole and betamethasone dipropionate cream showed a better clinical response at the first return visit than subjects treated with clotrimazole cream. In tinea corporis and tinea cruris, the subject returned 3 to 5 days after starting treatment, and in tinea pedis, after 1 week. Mycological cure rates observed in subjects treated with clotrimazole and betamethasone dipropionate cream were as good as, or better than, in those subjects treated with clotrimazole cream. In these same clinical studies, patients treated with clotrimazole and betamethasone dipropionate cream showed better clinical responses and mycological cure rates when compared with subjects treated with betamethasone dipropionate cream.

16 HOW SUPPLIED/STORAGE AND HANDLING

NDC:50436-0898-1 15 g in a TUBE

STORAGE AND HANDLING

Clotrimazole and betamethasone dipropionate cream is white to off-white and supplied in 15-gram (NDC 66993-898-15) and 45-gram tubes (NDC 66993-898-45), boxes of one. Store at 20-25°C (68-77°F); excursions permitted to 15-30°C (59-86°F) [see USP Controlled Room Temperature].

Rx only

17 PATIENT COUNSELING INFORMATION

See FDA-Approved Patient Labeling (Patient Information)

Inform the patient of the following:

- Use clotrimazole and betamethasone dipropionate cream as directed by the physician. It is for external use only.
- Avoid contact with the eyes, the mouth, or intravaginally.
- Do not use clotrimazole and betamethasone dipropionate cream on the face or underarms.
- Do not use more than 45 grams of clotrimazole and betamethasone dipropionate cream per week.
- When using clotrimazole and betamethasone dipropionate cream in the groin area, patients should use the medication for 2 weeks only, and apply the cream sparingly. Patients should wear loose-fitting clothing. Notify the physician if the condition persists after 2 weeks.
- Do not use clotrimazole and betamethasone dipropionate cream for any disorder other than that for which it was prescribed.
- Do not bandage, cover or wrap the treatment area unless directed by the physician. Avoid use of clotrimazole and betamethasone dipropionate cream in the diaper area, as diapers or plastic pants may constitute occlusive dressing.
- Report any signs of local adverse reactions to the physician. Advise patients that local reactions and skin atrophy are more likely to occur with occlusive use or prolonged use.
- This medication is to be used for the full prescribed treatment time, even though the symptoms may have improved. Notify the physician if there is no improvement after 1 week of treatment for tinea cruris or tinea corporis, or after 2 weeks for tinea pedis.

Manufactured for:
Prasco Laboratories
Mason, OH 45040, USA

Manufactured by:
Bayer Inc., Pointe Claire, Quebec H9R 1B4, Canada

Revised: 8/2015

uspi-gmk5335A-cr-1508r002

Patient Information

Clotrimazole and betamethasone dipropionate cream, 1%/0.05%

Important information: Clotrimazole and betamethasone dipropionate cream is for use on skin only. Do not use clotrimazole and betamethasone dipropionate cream in your eyes, mouth, or vagina.

What is clotrimazole and betamethasone dipropionate cream?

- Clotrimazole and betamethasone dipropionate cream is a prescription medication used on the skin (topical) to treat fungal infections of the feet, groin, and body in people 17 years of age and older. Clotrimazole and betamethasone dipropionate cream is used for fungal infections that are inflamed and have symptoms of redness or itching.
- Clotrimazole and betamethasone dipropionate cream should not be used in children under 17 years of age.

Before using clotrimazole and betamethasone dipropionate cream, tell your healthcare provider about all your medical conditions, including if you:

- are pregnant or plan to become pregnant. It is not known if clotrimazole and betamethasone dipropionate cream will harm your unborn baby.
- are breastfeeding or plan to breastfeed. It is not known if clotrimazole and betamethasone dipropionate cream passes into your breast milk.

Tell your healthcare provider about all the medicines you take, including prescription and over-the-counter medicines, vitamins, and herbal supplements. Especially tell your healthcare provider if you take other corticosteroid medicines by mouth or use other products on your skin or scalp that contain corticosteroids.

What should I avoid while using clotrimazole and betamethasone dipropionate cream?

Clotrimazole and betamethasone dipropionate cream should not be used to treat diaper rash or redness. You should avoid applying clotrimazole and betamethasone dipropionate cream in the diaper area.

How should I use clotrimazole and betamethasone dipropionate cream?

- Use clotrimazole and betamethasone dipropionate cream exactly as your healthcare provider tells you to use it.
- Use clotrimazole and betamethasone dipropionate cream for the prescribed treatment time, even if your symptoms get better.
- Do not use more than 45 grams of clotrimazole and betamethasone dipropionate cream in 1 week.
- Do not bandage, cover, or wrap the treated area unless your healthcare provider tells you to. Wear loose-fitting clothing if you use clotrimazole and betamethasone dipropionate cream in the groin area.
- Do not use clotrimazole and betamethasone dipropionate cream on your face or underarms (armpits).
- For treatment of fungal infections of the groin and body:
  - Apply a thin layer of clotrimazole and betamethasone dipropionate cream to the affected skin area 2 times a day for 1 week.
  - Tell your healthcare provider if the treated skin area does not improve after 1 week of treatment.
  - Do not use clotrimazole and betamethasone dipropionate cream for longer than 2 weeks.
- For treatment of fungal infections of the feet:
  - Apply a thin layer of clotrimazole and betamethasone dipropionate cream to the affected skin area 2 times a day for 2 weeks.
  - Tell your healthcare provider if the treated skin area does not improve after 2 weeks of treatment. Do not use clotrimazole and betamethasone dipropionate cream longer than 4 weeks.
  - Wash your hands after applying clotrimazole and betamethasone dipropionate cream.

What are the possible side effects of clotrimazole and betamethasone dipropionate cream?

Clotrimazole and betamethasone dipropionate cream may cause serious side effects, including:

- Clotrimazole and betamethasone dipropionate cream can pass through your skin. Too much clotrimazole and betamethasone dipropionate cream passing through your skin can cause your adrenal glands to stop working. Your healthcare provider may do blood tests to check for adrenal gland problems.

The most common side effects of clotrimazole and betamethasone dipropionate cream include burning, tingling, rash, swelling, and infections.

These are not all the possible side effects of clotrimazole and betamethasone dipropionate cream.

Call your doctor for medical advice about side effects. You may report side effects to FDA at 1-800-FDA-1088.

How should I store clotrimazole and betamethasone dipropionate cream?

- Store clotrimazole and betamethasone dipropionate cream at room temperature between 68 to 77°F (20 to 25°C)
- Keep clotrimazole and betamethasone dipropionate cream and all medicines out of the reach of children.

General information about the safe and effective use of clotrimazole and betamethasone dipropionate cream.

Medicines are sometimes prescribed for purposes other than those listed in a Patient Information leaflet. You can ask your pharmacist or healthcare provider for information about clotrimazole and betamethasone dipropionate cream that is written for health professionals. Do not use clotrimazole and betamethasone dipropionate cream for a condition for which it was not prescribed. Do not give clotrimazole and betamethasone dipropionate cream to other people, even if they have the same symptoms that you have. It may harm them.

What are the ingredients in clotrimazole and betamethasone dipropionate cream?

Active ingredients: clotrimazole and betamethasone dipropionate

Inactive ingredients: benzyl alcohol as a preservative, ceteareth-30, cetyl alcohol plus stearyl alcohol, mineral oil, phosphoric acid, propylene glycol, purified water, sodium phosphate monobasic monohydrate, and white petrolatum

Manufactured for:
Prasco Laboratories
Mason, OH 45040, USA

Manufactured by:
Bayer Inc., Pointe Claire, Quebec H9R 1B4, Canada

Revised: August 2015

usppi-gmk5335A-cr-1508r002